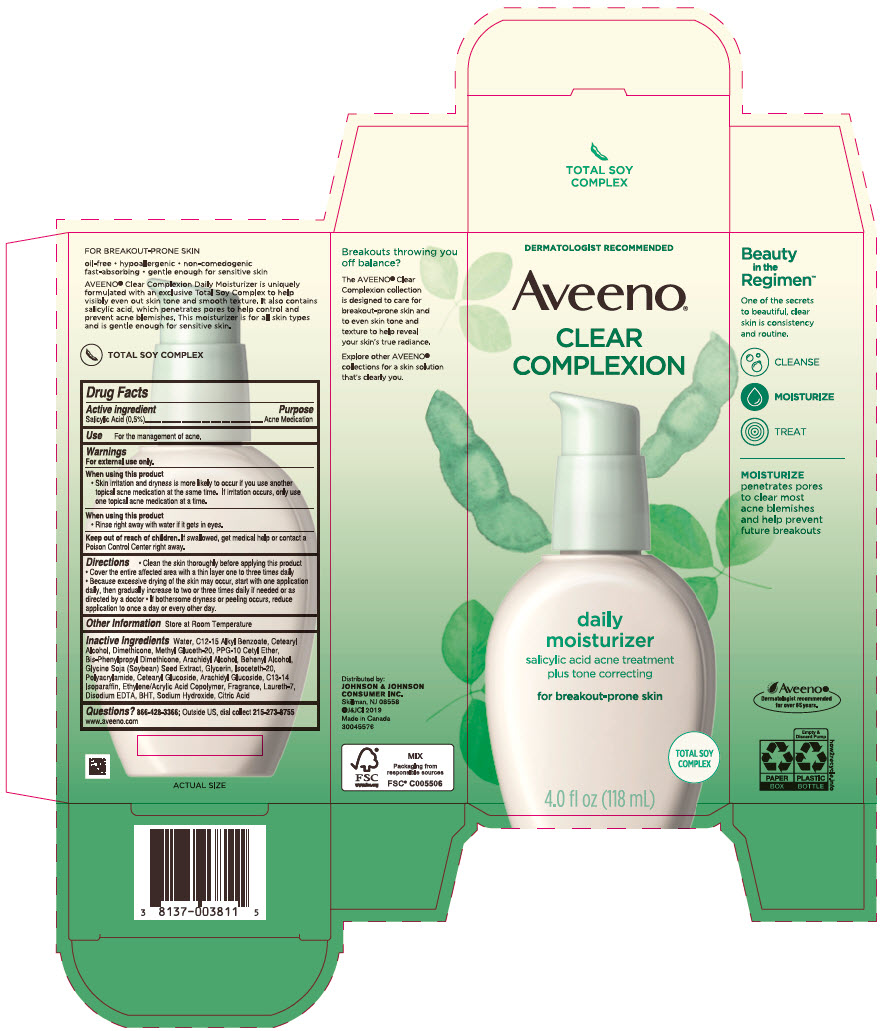 DRUG LABEL: Aveeno clear complexion daily moisturizer
NDC: 69968-0372 | Form: LOTION
Manufacturer: Kenvue Brands LLC
Category: otc | Type: HUMAN OTC DRUG LABEL
Date: 20240912

ACTIVE INGREDIENTS: SALICYLIC ACID 5 mg/1 mL
INACTIVE INGREDIENTS: WATER; ALKYL (C12-15) BENZOATE; CETOSTEARYL ALCOHOL; BIS-PHENYLPROPYL DIMETHICONE (15 CST); PPG-10 CETYL ETHER; METHYL GLUCETH-20; DIMETHICONE; ARACHIDYL ALCOHOL; SOYBEAN; ISOCETETH-20; DOCOSANOL; GLYCERIN; CETEARYL GLUCOSIDE; ARACHIDYL GLUCOSIDE; C13-14 ISOPARAFFIN; ACRYLIC ACID/ETHYLENE COPOLYMER (600 MPA.S); LAURETH-7; SODIUM HYDROXIDE; CITRIC ACID MONOHYDRATE; EDETATE DISODIUM ANHYDROUS; BUTYLATED HYDROXYTOLUENE

Aveeno® Clear Complexion daily moisturizer

Drug Facts

Active ingredient

Salicylic Acid 0.5%

Purpose

Acne Medication

Use

For the management of acne.

Warnings

For external use only.

When using this product

- Skin irritation and dryness is more likely to occur if you use another topical acne medication at the same time. If irritation occurs, only use one topical acne medication at a time.

When using this product

- Rinse right away with water if it gets in eyes.

Keep out of reach of children. If swallowed, get medical help or contact a Poison Control Center right away.

Directions

- Clean the skin thoroughly before applying this product
- Cover the entire affected area with a thin layer one to three times daily
- Because excessive drying of the skin may occur, start with one application daily, then gradually increase to two or three times daily if needed or as directed by a doctor
- If bothersome dryness or peeling occurs, reduce application to once a day or every other day.

Other information

- Store at Room Temperature

Inactive ingredients

Water, C12-15 Alkyl Benzoate, Cetearyl Alcohol, Dimethicone, Methyl Gluceth-20, PPG-10 Cetyl Ether, Bis-Phenylpropyl Dimethicone, Arachidyl Alcohol, Behenyl Alcohol, Glycine Soja (Soybean) Seed Extract, Glycerin, Isoceteth-20, Polyacrylamide, Cetearyl Glucoside, Arachidyl Glucoside, C13-14 Isoparaffin, Ethylene/Acrylic Acid Copolymer, Fragrance, Laureth-7, Disodium EDTA, BHT, Sodium Hydroxide, Citric Acid

Questions?

866-428-3366; Outside US, dial collect 215-273-8755 www.aveeno.com

Distributed by:
JOHNSON & JOHNSON
CONSUMER INC.
Skillman, NJ 08558

PRINCIPAL DISPLAY PANEL - 118 mL Bottle Carton

DERMATOLOGIST RECOMMENDED

Aveeno®

CLEAR
COMPLEXION

daily
moisturizer
salicylic acid acne treatment
plus tone correcting

for breakout-prone skin

TOTAL SOY
COMPLEX

4.0 fl oz (118mL)